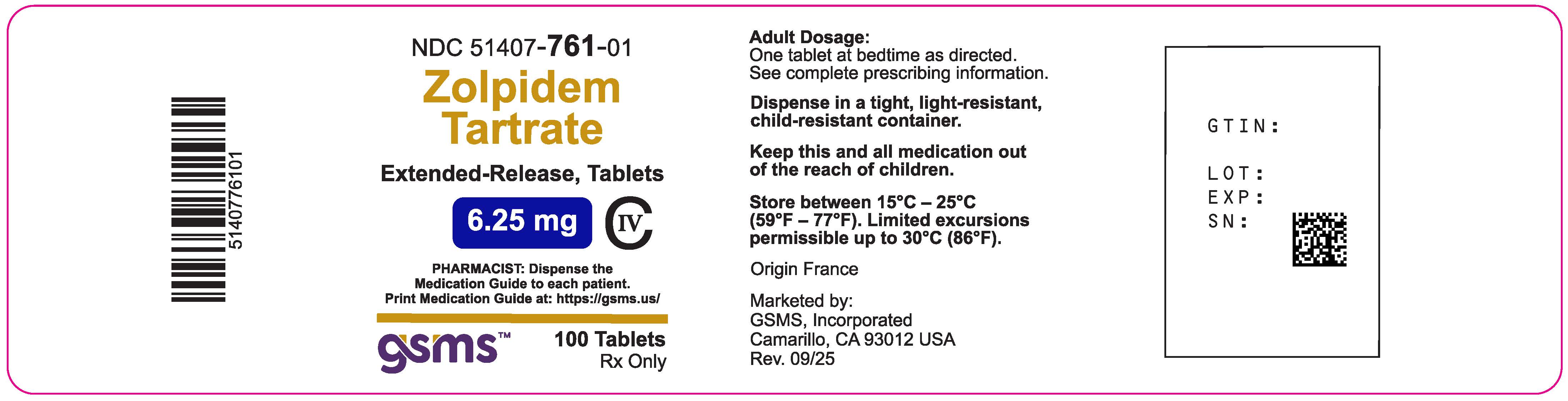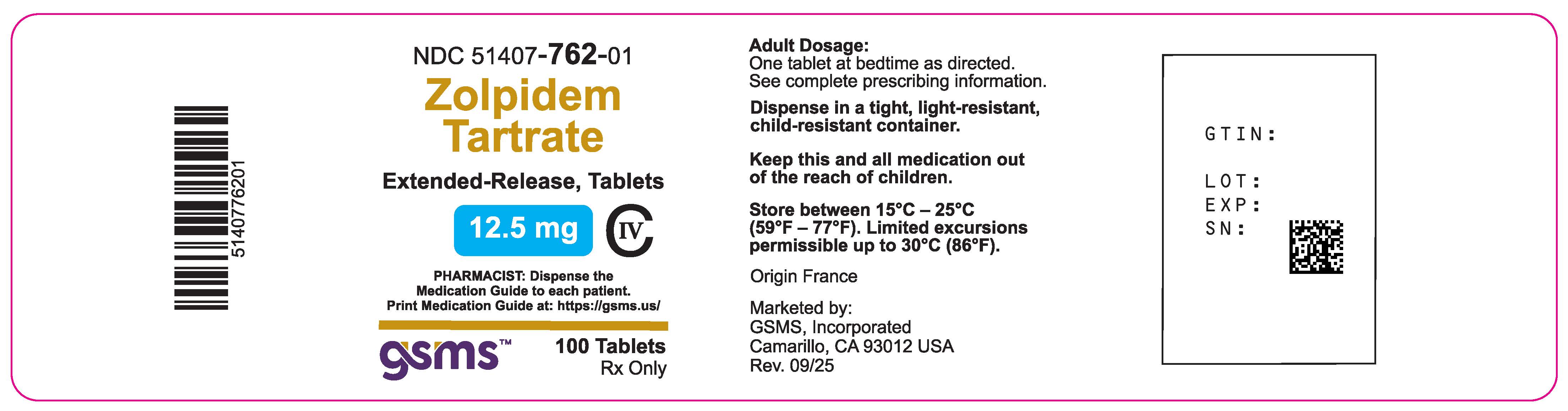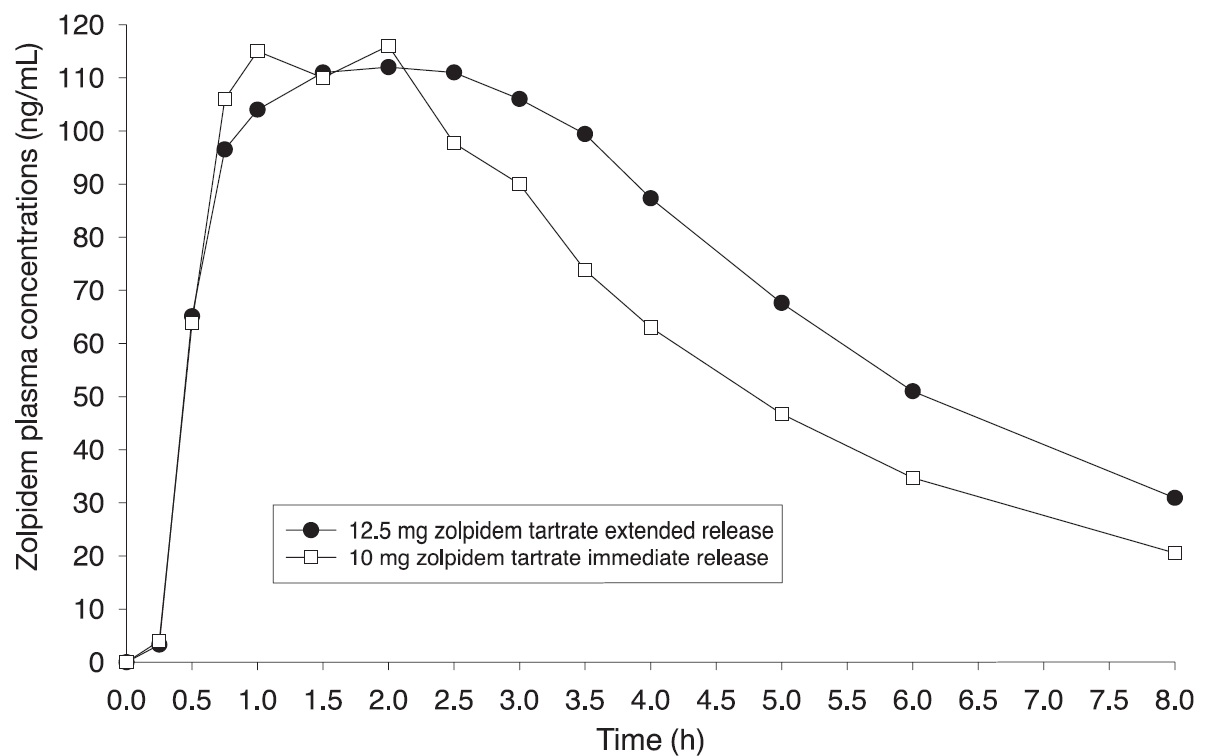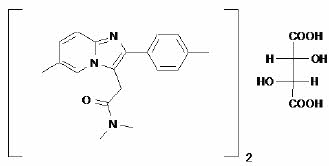 DRUG LABEL: zolpidem tartrate
NDC: 51407-762 | Form: TABLET, COATED
Manufacturer: Golden State Medical Supply, Inc.
Category: prescription | Type: HUMAN PRESCRIPTION DRUG LABEL
Date: 20251119
DEA Schedule: CIV

ACTIVE INGREDIENTS: ZOLPIDEM TARTRATE 12.5 mg/1 1
INACTIVE INGREDIENTS: SILICON DIOXIDE; FD&C BLUE NO. 2; HYPROMELLOSE, UNSPECIFIED; LACTOSE MONOHYDRATE; MAGNESIUM STEARATE; MICROCRYSTALLINE CELLULOSE; POLYETHYLENE GLYCOL, UNSPECIFIED; POTASSIUM BITARTRATE; TITANIUM DIOXIDE; FERRIC OXIDE YELLOW; SODIUM STARCH GLYCOLATE TYPE A CORN

HIGHLIGHTS OF PRESCRIBING INFORMATION

Zolpidem Tartrate Extended-Release Tablets. These highlights do not include all the information needed to use Zolpidem Tartrate safely and effectively. See full prescribing information for Zolpidem Tartrate.
Zolpidem Tartrate Extended-Release Tablets, for oral use, C-IV
Initial U.S. Approval: 1992

WARNING: COMPLEX SLEEP BEHAVIORS

See full prescribing information for complete boxed warning.

Complex sleep behaviors including sleep-walking, sleep-driving, and engaging in other activities while not fully awake may occur following use of Zolpidem Tartrate. Some of these events may result in serious injuries, including death. Discontinue Zolpidem Tartrate immediately if a patient experiences a complex sleep behavior. (4, 5.1)

RECENT MAJOR CHANGES

Indications and Usage (1) | 2/2022
Dosage and Administration (2.1) | 2/2022
Warnings and Precautions (5.5) | 2/2022
Warnings and Precautions (5.7) | 2/2022

1 INDICATIONS AND USAGE

Zolpidem Tartrate, a gamma-aminobutyric acid (GABA) A receptor positive modulator, is indicated for the short-term treatment of insomnia characterized by difficulties with sleep onset and/or sleep maintenance. (1)

2 DOSAGE AND ADMINISTRATION

- Use the lowest dose effective for the patient and must not exceed a total of 12.5 mg daily (2.1)
- Treatment should be as short as possible (2.1)
- Recommended initial dose is a single dose of 6.25 mg for women and a single dose of 6.25 or 12.5 mg for men, immediately before bedtime with at least 7–8 hours remaining before the planned time of awakening (2.1)
- Geriatric patients and patients with mild to moderate hepatic impairment: Recommended dose is 6.25 mg for men and women (2.2)
- Lower doses of CNS depressants may be necessary when taken concomitantly with AMBIEN CR (2.3)
- Tablets to be swallowed whole, not to be crushed, divided or chewed (2.4)
- The effect of AMBIEN CR may be slowed if taken with or immediately after a meal (2.4)

3 DOSAGE FORMS AND STRENGTHS

Extended-Release Tablets: 6.25 mg and 12.5 mg. Tablets notscored. (3)

4 CONTRAINDICATIONS

- Patients who have experienced complex sleep behaviors after taking Zolpidem Tartrate (4)
- Known hypersensitivity to zolpidem (4)

5 WARNINGS AND PRECAUTIONS

- CNS-Depressant Effects: Impaired alertness and motor coordination, including risk of morning impairment. Risk increases with dose and use with other CNS depressants and alcohol. Caution patients against driving and other activities requiring complete mental alertness the morning after use. Instruct patients on correct use. (5.2)
- Need to Evaluate for Comorbid Diagnoses: Reevaluate if insomnia persists after 7 to 10 days of use. (5.3)
- Severe Anaphylactic/Anaphylactoid Reactions: Angioedema and anaphylaxis have been reported. Do not rechallenge if such reactions occur. (5.4)
- Abnormal Thinking and Behavioral Changes: Changes including decreased inhibition, bizarre behavior, agitation, and depersonalization have been reported. Immediately evaluate any new onset behavioral changes. (5.5)
- Depression: Worsening of depression or suicidal thinking may occur. Prescribe the least amount of tablets feasible to avoid intentional overdose. (5.6)
- Respiratory Depression: Consider this risk before prescribing in patients with compromised respiratory function. (5.7)
- Hepatic Impairment: Avoid AMBIEN CR use in patients with severe hepatic impairment. (5.8)
- Withdrawal Effects: Symptoms may occur with rapid dose reduction or discontinuation. (5.9, 9.3)

6 ADVERSE REACTIONS

Most commonly observed adverse reactions (>10% in either elderly or adult patients) are: headache, next-day somnolence and dizziness (6.1)

To report SUSPECTED ADVERSE REACTIONS, contact Cosette Pharmaceuticals, Inc. at 1-800-922-1038 or FDA at 1-800-FDA-1088 or www.fda.gov/medwatch.

7 DRUG INTERACTIONS

- CNS depressants, including alcohol: Possible adverse additive CNS-depressant effects (5.2, 7.1)
- Opioids: Concomitant use may increase risk of respiratory depression (5.7, 7.1)
- Imipramine: Decreased alertness observed (7.1)
- Chlorpromazine: Impaired alertness and psychomotor performance observed (7.1)
- CYP3A4 inducers (rifampin or St. John's wort): Combination use may decrease effect (7.2)
- Ketoconazole: Combination use may increase effect (7.2)

8 USE IN SPECIFIC POPULATIONS

- Pregnancy: May cause respiratory depression and sedation in neonates with exposure late in the third trimester. (8.1)
- Lactation: A lactating woman may pump and discard breast milk during treatment and for 23 hours after AMBIEN CR administration. (8.2)
- Pediatric use: Safety and effectiveness not established. Hallucinations (incidence rate 7%) and other psychiatric and/or nervous system adverse reactions were observed frequently in a study of pediatric patients with Attention-Deficit/Hyperactivity Disorder. (5.5, 8.4)

FULL PRESCRIBING INFORMATION

WARNING: COMPLEX SLEEP BEHAVIORS

Complex sleep behaviors including sleep-walking, sleep-driving, and engaging in other activities while not fully awake may occur following use of Zolpidem Tartrate. Some of these events may result in serious injuries, including death. Discontinue Zolpidem Tartrate immediately if a patient experiences a complex sleep behavior [see Contraindications (4)and Warnings and Precautions (5.1)].

1 INDICATIONS AND USAGE

Zolpidem tartrate extended-release tablets is indicated for the short-term treatment of insomnia characterized by difficulties with sleep onset and/or sleep maintenance (as measured by wake time after sleep onset).

The clinical trials performed in support of efficacy were up to 3 weeks (using polysomnography measurement up to 2 weeks in both adult and elderly patients) and 24 weeks (using patient reported assessment in adult patients only) in duration [see Clinical Studies (14)].

2 DOSAGE AND ADMINISTRATION

2.1 Dosage in Adults

Use the lowest effective dose for the patient. The recommended initial dose is 6.25 mg for women and either 6.25 or 12.5 mg for men, taken only once per night immediately before bedtime with at least 7–8 hours remaining before the planned time of awakening. If the 6.25 mg dose is not effective, the dose can be increased to 12.5 mg. In some patients, the higher morning blood levels following use of the 12.5 mg dose increase the risk of next-day impairment of driving and other activities that require full alertness [see Warnings and Precautions (5.2)] . The total dose of Zolpidem Tartrate should not exceed 12.5 mg once daily immediately before bedtime. AZolpidem Tartrate should be taken as a single dose and should not be readministered during the same night.

The recommended initial doses for women and men are different because zolpidem clearance is lower in women.

Treatment with Zolpidem Tartrate should be as short as possible. Extended treatment should not take place without re-evaluation of the patient’s status, since the risk of abuse and dependence increases with duration of treatment [see Drug Abuse and Dependence (9.3)].

2.2 Special Populations

Elderly or debilitated patients may be especially sensitive to the effects of zolpidem tartrate. The recommended dose of Zolpidem Tartrate in these patients is 6.25 mg once daily immediately before bedtime [see Warnings and Precautions (5.2), Use in Specific Populations (8.5)].

Patients with mild to moderate hepatic impairment do not clear the drug as rapidly as normal subjects. The recommended dose of Zolpidem Tartrate in these patients is 6.25 mg once daily immediately before bedtime. Avoid Zolpidem Tartrate use in patients with severe hepatic impairment as it may contribute to encephalopathy [see Warnings and Precautions (5.8), Use in Specific Populations (8.7), Clinical Pharmacology (12.3)] .

2.3 Use with CNS Depressants

Dosage adjustment may be necessary when Zolpidem Tartrate is combined with other CNS-depressant drugs because of the potentially additive effects [see Warnings and Precautions (5.2, 5.7)] .

2.4 Administration

Zolpidem Tartrate extended-release tablets should be swallowed whole, and not be divided, crushed, or chewed. The effect of Zolpidem Tartrate may be slowed by ingestion with or immediately after a meal.

3 DOSAGE FORMS AND STRENGTHS

Zolpidem Tartrate is available as extended-release tablets containing 6.25 mg or 12.5 mg of zolpidem tartrate for oral administration. Tablets are not scored.

Zolpidem Tartrate 6.25 mg tablets are pink, round, bi-convex, and debossed with A~ on one side.

Zolpidem Tartrate 12.5 mg tablets are blue, round, bi-convex, and debossed with A~ on one side.

4 CONTRAINDICATIONS

Zolpidem Tartrate is contraindicated in patients

- who have experienced complex sleep behaviors after taking Zolpidem Tartrate [see Warnings and Precautions (5.1)].
- with known hypersensitivity to zolpidem. Observed reactions include anaphylaxis and angioedema [see Warnings and Precautions (5.4)].

5 WARNINGS AND PRECAUTIONS

5.1 Complex Sleep Behaviors

Complex sleep behaviors, including sleep-walking, sleep-driving, and engaging in other activities while not fully awake, may occur following the first or any subsequent use of Zolpidem Tartrate. Patients can be seriously injured or injure others during complex sleep behaviors. Such injuries may result in a fatal outcome. Other complex sleep behaviors (e.g., preparing and eating food, making phone calls, or having sex) have also been reported. Patients usually do not remember these events. Postmarketing reports have shown that complex sleep behaviors may occur with Zolpidem Tartrate alone at recommended doses, with or without the concomitant use of alcohol or other central nervous system (CNS) depressants [see Drug Interactions (7.1)] . Discontinue Zolpidem Tartrate immediately if a patient experiences a complex sleep behavior [see Contraindications (4)] .

5.2 CNS-Depressant Effects and Next-Day Impairment

Zolpidem Tartrate is a CNS depressant and can impair daytime function in some patients even when used as prescribed. Prescribers should monitor for excess depressant effects, but impairment can occur in the absence of subjective symptoms, and may not be reliably detected by ordinary clinical exam (i.e. less than formal psychomotor testing). While pharmacodynamic tolerance or adaptation to some adverse depressant effects of Zolpidem Tartrate may develop, patients using Zolpidem Tartrate should be cautioned against driving or engaging in other hazardous activities or activities requiring complete mental alertness the day after use.

Additive effects occur with concomitant use of other CNS depressants (e.g., benzodiazepines, opioids, tricyclic antidepressants, alcohol), including daytime use [see Drug Interactions (7.1)] . Downward dose adjustment of Zolpidem Tartrate and concomitant CNS depressants should be considered [see Dosage and Administration (2.3)] .

The use of Zolpidem Tartrate with other sedative-hypnotics (including other zolpidem products) at bedtime or the middle of the night is not recommended.

The risk of next-day psychomotor impairment is increased if Zolpidem Tartrate is taken with less than a full night of sleep remaining (7 to 8 hours); if higher than the recommended dose is taken; if coadministered with other CNS depressants or alcohol; or coadministered with other drugs that increase the blood levels of zolpidem. Patients should be warned against driving and other activities requiring complete mental alertness if Zolpidem Tartrate is taken in these circumstances [see Dosage and Administration (2), Clinical Studies (14.2)] .

Vehicle drivers and machine operators should be warned that, as with other hypnotics, there may be a possible risk of adverse reactions including drowsiness, prolonged reaction time, dizziness, sleepiness, blurred/double vision, reduced alertness, and impaired driving the morning after therapy. In order to minimize this risk a full night of sleep (7–8 hours) is recommended.

Because Zolpidem Tartrate can cause drowsiness and a decreased level of consciousness, patients, particularly the elderly, are at higher risk of falls.

5.3 Need to Evaluate for Comorbid Diagnoses

Because sleep disturbances may be the presenting manifestation of a physical and/or psychiatric disorder, symptomatic treatment of insomnia should be initiated only after a careful evaluation of the patient. The failure of insomnia to remit after 7 to 10 days of treatment may indicate the presence of a primary psychiatric and/or medical illness that should be evaluated. Worsening of insomnia or the emergence of new thinking or behavior abnormalities may be the consequence of an unrecognized psychiatric or physical disorder. Such findings have emerged during the course of treatment with sedative/hypnotic drugs, including zolpidem.

5.4 Severe Anaphylactic and Anaphylactoid Reactions

Cases of angioedema involving the tongue, glottis or larynx have been reported in patients after taking the first or subsequent doses of sedative-hypnotics, including zolpidem. Some patients have had additional symptoms such as dyspnea, throat closing or nausea and vomiting that suggest anaphylaxis. Some patients have required medical therapy in the emergency department. If angioedema involves the throat, glottis or larynx, airway obstruction may occur and be fatal. Patients who develop angioedema after treatment with zolpidem should not be rechallenged with the drug.

5.5 Abnormal Thinking and Behavioral Changes

Abnormal thinking and behavior changes have been reported in patients treated with sedative/hypnotics, including Zolpidem Tartrate. Some of these changes included decreased inhibition (e.g., aggressiveness and extroversion that seemed out of character), bizarre behavior, agitation and depersonalization. Visual and auditory hallucinations have been reported.

In controlled trials, <1% of adults with insomnia reported hallucinations. In a clinical trial, 7% of pediatric patients treated with Zolpidem Tartrate 0.25 mg/kg taken at bedtime reported hallucinations versus 0% treated with placebo [see Use in Specific Populations (8.4)]. There have been postmarketing reports of delirium with zolpidem use [see Adverse Reactions (6.2)].

It can rarely be determined with certainty whether a particular instance of the abnormal behaviors listed above is drug induced, spontaneous in origin, or a result of an underlying psychiatric or physical disorder. Nonetheless, the emergence of any new behavioral sign or symptom of concern requires careful and immediate evaluation.

5.6 Use in Patients with Depression

In primarily depressed patients treated with sedative-hypnotics, worsening of depression, and suicidal thoughts and actions (including completed suicides), have been reported. Suicidal tendencies may be present in such patients and protective measures may be required. Intentional overdosage is more common in this group of patients; therefore, the lowest number of tablets that is feasible should be prescribed for the patient at any one time.

5.7 Respiratory Depression

Although studies with 10 mg zolpidem tartrate did not reveal respiratory depressant effects at hypnotic doses in healthy subjects or in patients with mild to moderate chronic obstructive pulmonary disease (COPD), a reduction in the Total Arousal Index, together with a reduction in lowest oxygen saturation and increase in the times of oxygen desaturation below 80% and 90%, was observed in patients with mild to moderate sleep apnea when treated with zolpidem compared to placebo. Since sedative-hypnotics have the capacity to depress respiratory drive, precautions should be taken if Zolpidem Tartrate is prescribed to patients with compromised respiratory function or concomitant use with opioids or other CNS depressants. Postmarketing reports of respiratory insufficiency in patients receiving 10 mg of zolpidem tartrate, most of whom had pre-existing respiratory impairment, have been reported. The risk of respiratory depression should be considered prior to prescribing Zolpidem Tartrate in patients with respiratory impairment including sleep apnea and myasthenia gravis or with concomitant opioid use [see Dosage and Administration (2.3), Drug Interactions (7.1)].

5.8 Precipitation of Hepatic Encephalopathy

Drugs affecting GABA receptors, such as zolpidem tartrate, have been associated with precipitation of hepatic encephalopathy in patients with hepatic insufficiency. In addition, patients with hepatic insufficiency do not clear zolpidem tartrate as rapidly as patients with normal hepatic function. Avoid Zolpidem Tartrate use in patients with severe hepatic impairment as it may contribute to encephalopathy [see Dosage and Administration (2.2), Use in Specific Populations (8.7), Clinical Pharmacology (12.3)] .

5.9 Withdrawal Effects

There have been reports of withdrawal signs and symptoms following the rapid dose decrease or abrupt discontinuation of zolpidem. Monitor patients for tolerance, abuse, and dependence [see Drug Abuse and Dependence (9.2, 9.3)] .

6 ADVERSE REACTIONS

The following serious adverse reactions are discussed in greater detail in other sections of the labeling:

- Complex Sleep Behaviors [see Warnings and Precautions (5.1)]
- CNS-Depressant Effects and Next-Day Impairment [see Warnings and Precautions (5.2)]
- Severe Anaphylactic and Anaphylactoid Reactions [see Warnings and Precautions (5.4)]
- Abnormal Thinking and Behavior Changes [see Warnings and Precautions (5.5)]
- Withdrawal Effects [see Warnings and Precautions (5.9)]

6.1 Clinical Trials Experience

Associated with Discontinuation of Treatment

In 3-week clinical trials in adults and elderly patients (>65 years), 3.5% (7/201) patients receiving Zolpidem Tartrate 6.25 or 12.5 mg discontinued treatment due to an adverse reaction as compared to 0.9% (2/216) of patients on placebo. The reaction most commonly associated with discontinuation in patients treated with Zolpidem Tartrate was somnolence (1%).

In a 6-month study in adult patients (18–64 years of age), 8.5% (57/669) of patients receiving Zolpidem Tartrate 12.5 mg as compared to 4.6% on placebo (16/349) discontinued treatment due to an adverse reaction. Reactions most commonly associated with discontinuation of Zolpidem Tartrate included anxiety (anxiety, restlessness or agitation) reported in 1.5% (10/669) of patients as compared to 0.3% (1/349) of patients on placebo, and depression (depression, major depression or depressed mood) reported in 1.5% (10/669) of patients as compared to 0.3% (1/349) of patients on placebo.

Data from a clinical study in which selective serotonin reuptake inhibitor (SSRI)-treated patients were given zolpidem revealed that four of the seven discontinuations during double-blind treatment with zolpidem (n=95) were associated with impaired concentration, continuing or aggravated depression, and manic reaction; one patient treated with placebo (n=97) was discontinued after an attempted suicide.

Most Commonly Observed Adverse Reactions in Controlled Trials

During treatment with Zolpidem Tartrate in adults and elderly at daily doses of 12.5 mg and 6.25 mg, respectively, each for three weeks, the most commonly observed adverse reactions associated with the use of Zolpidem Tartrate were headache, next-day somnolence, and dizziness.

In the 6-month trial evaluating Zolpidem Tartrate 12.5 mg, the adverse reaction profile was consistent with that reported in short-term trials, except for a higher incidence of anxiety (6.3% for Zolpidem Tartrate versus 2.6% for placebo).

Adverse Reactions Observed at an Incidence of ≥1% in Controlled Trials

The following tables enumerate treatment-emergent adverse reactions frequencies that were observed at an incidence equal to 1% or greater among patients with insomnia who received Zolpidem Tartrate in placebo-controlled trials. Events reported by investigators were classified utilizing the MedDRA dictionary for the purpose of establishing event frequencies. The prescriber should be aware that these figures cannot be used to predict the incidence of side effects in the course of usual medical practice, in which patient characteristics and other factors differ from those that prevailed in these clinical trials. Similarly, the cited frequencies cannot be compared with figures obtained from other clinical investigators involving related drug products and uses, since each group of drug trials is conducted under a different set of conditions. However, the cited figures provide the physician with a basis for estimating the relative contribution of drug and nondrug factors to the incidence of side effects in the population studied.

The following tables were derived from results of two placebo-controlled efficacy trials involving Zolpidem Tartrate. These trials involved patients with primary insomnia who were treated for 3 weeks with Zolpidem Tartrate at doses of 12.5 mg (Table 1) or 6.25 mg (Table 2), respectively. The tables include only adverse reactions occurring at an incidence of at least 1% for Zolpidem Tartrate patients and with an incidence greater than that seen in the placebo patients.

Table 1: Incidences of Treatment-Emergent Adverse Reactions in a 3-Week Placebo-Controlled Clinical Trial in Adults (percentage of patients reporting)
Body System Adverse Reaction [Reactions reported by at least 1% of patients treated with Zolpidem Tartrate and at greater frequency than in the placebo group.] | Zolpidem Tartrate 12.5 mg | Placebo
Body System Adverse Reaction [Reactions reported by at least 1% of patients treated with Zolpidem Tartrate and at greater frequency than in the placebo group.] | (N=102) | (N=110)
Infections and infestations
Influenza | 3 | 0
Gastroenteritis | 1 | 0
Labyrinthitis | 1 | 0
Metabolism and nutrition disorders
Appetite disorder | 1 | 0
Psychiatric disorders
Hallucinations [Hallucinations included hallucinations NOS as well as visual and hypnagogic hallucinations.] | 4 | 0
Disorientation | 3 | 2
Anxiety | 2 | 0
Depression | 2 | 0
Psychomotor retardation | 2 | 0
Binge eating | 1 | 0
Depersonalization | 1 | 0
Disinhibition | 1 | 0
Euphoric mood | 1 | 0
Mood swings | 1 | 0
Stress symptoms | 1 | 0
Nervous system disorders
Headache | 19 | 16
Somnolence | 15 | 2
Dizziness | 12 | 5
Memory disorders [Memory disorders include: memory impairment, amnesia, anterograde amnesia.] | 3 | 0
Balance disorder | 2 | 0
Disturbance in attention | 2 | 0
Hypoesthesia | 2 | 1
Ataxia | 1 | 0
Paresthesia | 1 | 0
Eye disorders
Visual disturbance | 3 | 0
Eye redness | 2 | 0
Vision blurred | 2 | 1
Altered visual depth perception | 1 | 0
Asthenopia | 1 | 0
Ear and labyrinth disorders
Vertigo | 2 | 0
Tinnitus | 1 | 0
Respiratory, thoracic and mediastinal disorders
Throat irritation | 1 | 0
Gastrointestinal disorders
Nausea | 7 | 4
Constipation | 2 | 0
Abdominal discomfort | 1 | 0
Abdominal tenderness | 1 | 0
Frequent bowel movements | 1 | 0
Gastroesophageal reflux disease | 1 | 0
Vomiting | 1 | 0
Skin and subcutaneous tissue disorders
Rash | 1 | 0
Skin wrinkling | 1 | 0
Urticaria | 1 | 0
Musculoskeletal and connective tissue disorders
Back pain | 4 | 3
Myalgia | 4 | 0
Neck pain | 1 | 0
Reproductive system and breast disorders
Menorrhagia | 1 | 0
General disorders and administration site conditions
Fatigue | 3 | 2
Asthenia | 1 | 0
Chest discomfort | 1 | 0
Investigations
Blood pressure increased | 1 | 0
Body temperature increased | 1 | 0
Injury, poisoning and procedural complications
Contusion | 1 | 0
Social circumstances
Exposure to poisonous plant | 1 | 0

Table 2: Incidences of Treatment-Emergent Adverse Reactions in a 3-Week Placebo-Controlled Clinical Trial in Elderly (percentage of patients reporting)
Body System Adverse Reaction [Reactions reported by at least 1% of patients treated with Zolpidem Tartrate and at greater frequency than in the placebo group.] | Zolpidem Tartrate 6.25 mg | Placebo
Body System Adverse Reaction [Reactions reported by at least 1% of patients treated with Zolpidem Tartrate and at greater frequency than in the placebo group.] | (N=99) | (N=106)
Infections and infestations
Nasopharyngitis | 6 | 4
Lower respiratory tract infection | 1 | 0
Otitis externa | 1 | 0
Upper respiratory tract infection | 1 | 0
Psychiatric disorders
Anxiety | 3 | 2
Psychomotor retardation | 2 | 0
Apathy | 1 | 0
Depressed mood | 1 | 0
Nervous system disorders
Headache | 14 | 11
Dizziness | 8 | 3
Somnolence | 6 | 5
Burning sensation | 1 | 0
Dizziness postural | 1 | 0
Memory disorders [Memory disorders include: memory impairment, amnesia, anterograde amnesia.] | 1 | 0
Muscle contractions involuntary | 1 | 0
Paresthesia | 1 | 0
Tremor | 1 | 0
Cardiac disorders
Palpitations | 2 | 0
Respiratory, thoracic and mediastinal disorders
Dry throat | 1 | 0
Gastrointestinal disorders
Flatulence | 1 | 0
Vomiting | 1 | 0
Skin and subcutaneous tissue disorders
Rash | 1 | 0
Urticaria | 1 | 0
Musculoskeletal and connective tissue disorders
Arthralgia | 2 | 0
Muscle cramp | 2 | 1
Neck pain | 2 | 0
Renal and urinary disorders
Dysuria | 1 | 0
Reproductive system and breast disorders
Vulvovaginal dryness | 1 | 0
General disorders and administration site conditions
Influenza like illness | 1 | 0
Pyrexia | 1 | 0
Injury, poisoning and procedural complications
Neck injury | 1 | 0

Dose Relationship for Adverse Reactions

There is evidence from dose comparison trials suggesting a dose relationship for many of the adverse reactions associated with zolpidem use, particularly for certain CNS and gastrointestinal adverse events.

Other Adverse Reactions Observed during the Premarketing Evaluation of Zolpidem Tartrate

Other treatment-emergent adverse reactions associated with participation in Zolpidem Tartrate studies (those reported at frequencies of <1%) were not different in nature or frequency to those seen in studies with immediate-release zolpidem tartrate, which are listed below.

Adverse Events Observed during the Premarketing Evaluation of Immediate-Release Zolpidem Tartrate

Immediate-release zolpidem tartrate was administered to 3,660 subjects in clinical trials throughout the U.S., Canada, and Europe. Treatment-emergent adverse events associated with clinical trial participation were recorded by clinical investigators using terminology of their own choosing. To provide a meaningful estimate of the proportion of individuals experiencing treatment-emergent adverse events, similar types of untoward events were grouped into a smaller number of standardized event categories and classified utilizing a modified World Health Organization (WHO) dictionary of preferred terms.

The frequencies presented, therefore, represent the proportions of the 3,660 individuals exposed to zolpidem, at all doses, who experienced an event of the type cited on at least one occasion while receiving zolpidem. All reported treatment-emergent adverse events are included, except those already listed in the table above of adverse events in placebo-controlled studies, those coding terms that are so general as to be uninformative, and those events where a drug cause was remote. It is important to emphasize that, although the events reported did occur during treatment with Zolpidem Tartrate, they were not necessarily caused by it.

Adverse events are further classified within body system categories and enumerated in order of decreasing frequency using the following definitions: frequent adverse events are defined as those occurring in greater than 1/100 subjects; infrequent adverse events are those occurring in 1/100 to 1/1,000 patients; rare events are those occurring in less than 1/1,000 patients.

Autonomic nervous system:Frequent: dry mouth. Infrequent: increased sweating, pallor, postural hypotension, syncope. Rare: abnormal accommodation, altered saliva, flushing, glaucoma, hypotension, impotence, increased saliva, tenesmus.

Body as a whole:Frequent: asthenia. Infrequent: chest pain, edema, falling, fever, malaise, trauma. Rare: allergic reaction, allergy aggravated, anaphylactic shock, face edema, hot flashes, increased ESR, pain, restless legs, rigors, tolerance increased, weight decrease.

Cardiovascular system:Infrequent: cerebrovascular disorder, hypertension, tachycardia. Rare: angina pectoris, arrhythmia, arteritis, circulatory failure, extrasystoles, hypertension aggravated, myocardial infarction, phlebitis, pulmonary embolism, pulmonary edema, varicose veins, ventricular tachycardia.

Central and peripheral nervous system:Frequent: ataxia, confusion, drowsiness, drugged feeling, euphoria, insomnia, lethargy, lightheadedness, vertigo. Infrequent: agitation, decreased cognition, detached, difficulty concentrating, dysarthria, emotional lability, hallucination, hypoesthesia, illusion, leg cramps, migraine, nervousness, paresthesia, sleeping (after daytime dosing), speech disorder, stupor, tremor. Rare: abnormal gait, abnormal thinking, aggressive reaction, apathy, appetite increased, decreased libido, delusion, dementia, depersonalization, dysphasia, feeling strange, hypokinesia, hypotonia, hysteria, intoxicated feeling, manic reaction, neuralgia, neuritis, neuropathy, neurosis, panic attacks, paresis, personality disorder, somnambulism, suicide attempts, tetany, yawning.

Gastrointestinal system:Frequent: diarrhea, dyspepsia, hiccup. Infrequent: anorexia, constipation, dysphagia, flatulence, gastroenteritis. Rare: enteritis, eructation, esophagospasm, gastritis, hemorrhoids, intestinal obstruction, rectal hemorrhage, tooth caries.

Hematologic and lymphatic system:Rare: anemia, hyperhemoglobinemia, leukopenia, lymphadenopathy, macrocytic anemia, purpura, thrombosis.

Immunologic system:Infrequent: infection. Rare: abscess herpes simplex herpes zoster, otitis externa, otitis media.

Liver and biliary system:Infrequent: abnormal hepatic function, increased SGPT. Rare: bilirubinemia, increased SGOT.

Metabolic and nutritional:Infrequent: hyperglycemia, thirst. Rare: gout, hypercholesteremia, hyperlipidemia, increased alkaline phosphatase, increased BUN, periorbital edema.

Musculoskeletal system:Infrequent: arthritis. Rare: arthrosis, muscle weakness, sciatica, tendinitis.

Reproductive system:Infrequent: menstrual disorder, vaginitis. Rare: breast fibroadenosis, breast neoplasm, breast pain.

Respiratory system:Frequent: sinusitis. Infrequent: bronchitis, coughing, dyspnea. Rare: bronchospasm, respiratory depression, epistaxis, hypoxia, laryngitis, pneumonia.

Skin and appendages:Infrequent: pruritus. Rare: acne, bullous eruption, dermatitis, furunculosis, injection-site inflammation, photosensitivity reaction, urticaria.

Special senses:Frequent: diplopia, vision abnormal. Infrequent: eye irritation, eye pain, scleritis, taste perversion, tinnitus. Rare: conjunctivitis, corneal ulceration, lacrimation abnormal, parosmia, photopsia.

Urogenital system:Frequent: urinary tract infection. Infrequent: cystitis, urinary incontinence. Rare: acute renal failure, dysuria, micturition frequency, nocturia, polyuria, pyelonephritis, renal pain, urinary retention.

6.2 Postmarketing Experience

The following adverse reactions have been identified during postapproval use of Zolpidem Tartrate. Because these reactions are reported voluntarily from a population of uncertain size, it is not always possible to reliably estimate their frequency or establish a causal relationship to drug exposure.

Liver and biliary system:acute hepatocellular, cholestatic or mixed liver injury with or without jaundice (i.e., bilirubin >2 × ULN, alkaline phosphatase ≥2 × ULN, transaminase ≥5 × ULN).

Psychiatric disorders:delirium

7 DRUG INTERACTIONS

7.1 CNS-Active Drugs

CNS Depressants

Coadministration of zolpidem with other CNS depressants increases the risk of CNS depression. Concomitant use of zolpidem with these drugs may increase drowsiness and psychomotor impairment, including impaired driving ability [see Warnings and Precautions (5.1, 5.2)]. Zolpidem tartrate was evaluated in healthy volunteers in single-dose interaction studies for several CNS drugs.

Alcohol

An additive adverse effect on psychomotor performance between alcohol and oral zolpidem was demonstrated [see Warnings and Precautions (5.1, 5.2)] .

Opioids

The concomitant use of Zolpidem Tartrate with opioids may increase the risk of respiratory depression. Limit dosage and duration of concomitant use of Zolpidem Tartrate and opioids [see Dosage and Administration (2.3), Warnings and Precautions (5.7)] .

Imipramine, Chlorpromazine

Imipramine in combination with zolpidem produced no pharmacokinetic interaction other than a 20% decrease in peak levels of imipramine, but there was an additive effect of decreased alertness. Similarly, chlorpromazine in combination with zolpidem produced no pharmacokinetic interaction, but there was an additive effect of decreased alertness and psychomotor performance [see Clinical Pharmacology (12.3)] .

Sertraline

Concomitant administration of zolpidem and sertraline increases exposure to zolpidem [see Clinical Pharmacology (12.3)] .

Fluoxetine

After multiple doses of zolpidem tartrate and fluoxetine an increase in the zolpidem half-life (17%) was observed. There was no evidence of an additive effect in psychomotor performance [see Clinical Pharmacology (12.3)] .

Haloperidol

A study involving haloperidol and zolpidem revealed no effect of haloperidol on the pharmacokinetics or pharmacodynamics of zolpidem. The lack of a drug interaction following single-dose administration does not predict the absence of an effect following chronic administration [see Clinical Pharmacology (12.3)] .

7.2 Drugs that Affect Drug Metabolism via Cytochrome P450

Some compounds known to induce or inhibit CYP3A may affect exposure to zolpidem. The effect of drugs that induce or inhibit other P450 enzymes on the exposure to zolpidem is not known.

CYP3A4 Inducers

Rifampin

Rifampin, a CYP3A4 inducer, significantly reduced the exposure to and the pharmacodynamic effects of zolpidem. Use of Rifampin in combination with zolpidem may decrease the efficacy of zolpidem and is not recommended [see Clinical Pharmacology (12.3)] .

St. John's wort

Use of St. John's wort, a CYP3A4 inducer, in combination with zolpidem may decrease blood levels of zolpidem and is not recommended.

CYP3A4 Inhibitors

Ketoconazole

Ketoconazole, a potent CYP3A4 inhibitor, increased the exposure to and pharmacodynamic effects of zolpidem. Consideration should be given to using a lower dose of zolpidem when a potent CYP3A4 inhibitor and zolpidem are given together [see Clinical Pharmacology (12.3)] .

8 USE IN SPECIFIC POPULATIONS

8.1 Pregnancy

Risk Summary

Neonates born to mothers using zolpidem late in the third trimester of pregnancy have been reported to experience symptoms of respiratory depression and sedation [see Clinical Considerationsand Data] . Published data on the use of zolpidem during pregnancy have not reported a clear association with zolpidem and major birth defects [see Data] . Oral administration of zolpidem to pregnant rats and rabbits did not indicate a risk for adverse effects on fetal development at clinically relevant doses [see Data] .

The estimated background risk of major birth defects and miscarriage for the indicated populations are unknown. All pregnancies have a background risk of birth defect, loss, or other adverse outcomes. In the U.S. general population, the estimated background risk of major birth defects and miscarriage in clinically recognized pregnancies is 2%–4% and 15%–20%, respectively.

Clinical Considerations

Fetal/neonatal adverse reactions

Zolpidem crosses the placenta and may produce respiratory depression and sedation in neonates. Monitor neonates exposed to Zolpidem Tartrate during pregnancy and labor for signs of excess sedation, hypotonia, and respiratory depression and manage accordingly.

Data

Human data

Published data from observational studies, birth registries, and case reports on the use of zolpidem during pregnancy do not report a clear association with zolpidem and major birth defects.

There are limited postmarketing reports of severe to moderate cases of respiratory depression that occurred after birth in neonates whose mothers had taken zolpidem during pregnancy. These cases required artificial ventilation or intratracheal intubation. The majority of neonates recovered within hours to a few weeks after birth once treated.

Zolpidem has been shown to cross the placenta.

Animal data

Oral administration of zolpidem to pregnant rats during the period of organogenesis at 4, 20, and 100 mg base/kg/day, which are approximately 4, 20, and 100 times the maximum recommended human dose (MRHD) of 12.5 mg/day (10 mg zolpidem base) based on mg/m^2body surface area, caused delayed fetal development (incomplete fetal skeletal ossification) at maternally toxic (ataxia) doses 20 and 100 times the MRHD based on mg/m^2body surface area.

Oral administration of zolpidem to pregnant rabbits during the period of organogenesis at 1, 4, and 16 mg base/kg/day, which are approximately 2, 8, and 30 times the MRHD of 12.5 mg/day (10 mg zolpidem base) based on mg/m^2body surface area caused embryo-fetal death and delayed fetal development (incomplete fetal skeletal ossification) at a maternally toxic (decreased body weight gain) dose 30 times the MRHD based on mg/m^2body surface area.

Oral administration of zolpidem to pregnant rats from day 15 of gestation through lactation at 4, 20, and 100 mg base/kg/day, which are approximately 4, 20, and 100 times the MRHD of 12.5 mg/day (10 mg zolpidem base) based on a mg/m^2body surface area, delayed offspring growth and decreased survival at doses 20 and 100 times, respectively, the MRHD based on mg/m^2body surface area.

8.2 Lactation

Risk Summary

Limited data from published literature report the presence of zolpidem in human milk. There are reports of excess sedation in infants exposed to zolpidem through breastmilk [see Clinical Considerations]. There is no information on the effects of zolpidem on milk production. The developmental and health benefits of breastfeeding should be considered along with the mother's clinical need for Zolpidem Tartrate and any potential adverse effects on the breastfed infant from Zolpidem Tartrate or from the underlying maternal condition.

Clinical Considerations

Infants exposed to Zolpidem Tartrate through breastmilk should be monitored for excess sedation, hypotonia, and respiratory depression. A lactating woman may consider interrupting breastfeeding and pumping and discarding breast milk during treatment and for 23 hours (approximately 5 elimination half-lives) after Zolpidem Tartrate administration in order to minimize drug exposure to a breast fed infant.

8.4 Pediatric Use

Zolpidem Tartrate is not recommended for use in children. Safety and effectiveness of zolpidem in pediatric patients below the age of 18 years have not been established.

In an 8-week study in pediatric patients (aged 6–17 years) with insomnia associated with attention-deficit/hyperactivity disorder (ADHD) an oral solution of zolpidem tartrate dosed at 0.25 mg/kg at bedtime did not decrease sleep latency compared to placebo. Psychiatric and nervous system disorders comprised the most frequent (>5%) treatment emergent adverse reactions observed with zolpidem versus placebo and included dizziness (23.5% vs 1.5%), headache (12.5% vs 9.2%), and hallucinations were reported in 7% of the pediatric patients who received zolpidem; none of the pediatric patients who received placebo reported hallucinations [see Warnings and Precautions (5.5)] . Ten patients on zolpidem (7.4%) discontinued treatment due to an adverse reaction.

FDA has not required pediatric studies of Zolpidem Tartrate in the pediatric population based on these efficacy and safety findings.

8.5 Geriatric Use

A total of 99 elderly (≥65 years of age) received daily doses of 6.25 mg Zolpidem Tartrate in a 3-week placebo-controlled study. The adverse reaction profile of Zolpidem Tartrate 6.25 mg in this population was similar to that of Zolpidem Tartrate 12.5 mg in younger adults (≤64 years of age). Dizziness was reported in 8% of Zolpidem Tartrate–treated patients compared with 3% of those treated with placebo.

The dose of Zolpidem Tartrate in elderly patients is 6.25 mg to minimize adverse effects related to impaired motor and/or cognitive performance and unusual sensitivity to sedative/hypnotic drugs [see Warnings and Precautions (5.2)] .

8.6 Gender Difference in Pharmacokinetics

Women clear zolpidem tartrate from the body at a lower rate than men. Cmaxand AUC parameters of zolpidem from Zolpidem Tartrate were, respectively, approximately 50% and 75% higher at the same dose in adult female subjects compared to adult male subjects. Between 6 and 12 hours after dosing, zolpidem concentrations were 2 to 3 fold higher in adult female compared to adult male subjects. Given the higher blood levels of zolpidem tartrate in women compared to men at a given dose, the recommended initial dose of Zolpidem Tartrate for adult women is 6.25 mg, and the recommended dose for adult men is 6.25 or 12.5 mg.

In geriatric patients, clearance of zolpidem is similar in men and women. The recommended dose of Zolpidem Tartrate in geriatric patients is 6.25 mg regardless of gender.

8.7 Hepatic Impairment

The recommended dose of Zolpidem Tartrate in patients with mild to moderate hepatic impairment is 6.25 mg once daily immediately before bedtime. Avoid Zolpidem Tartrate use in patients with severe hepatic impairment as it may contribute to encephalopathy [see Dosage and Administration (2.2), Warnings and Precautions (5.8), Clinical Pharmacology (12.3)] .

9 DRUG ABUSE AND DEPENDENCE

9.1 Controlled Substance

Zolpidem tartrate is classified as a Schedule IV controlled substance by federal regulation.

9.2 Abuse

Abuse and addiction are separate and distinct from physical dependence and tolerance. Abuse is characterized by misuse of the drug for non-medical purposes, often in combination with other psychoactive substances. Tolerance is a state of adaptation in which exposure to a drug induces changes that result in a diminution of one or more of the drug effects over time. Tolerance may occur to both desired and undesired effects of drugs and may develop at different rates for different effects.

Addiction is a primary, chronic, neurobiological disease with genetic, psychosocial, and environmental factors influencing its development and manifestations. It is characterized by behaviors that include one or more of the following: impaired control over drug use, compulsive use, continued use despite harm, and craving. Drug addiction is a treatable disease, using a multidisciplinary approach, but relapse is common.

Studies of abuse potential in former drug abusers found that the effects of single doses of zolpidem tartrate 40 mg were similar, but not identical, to diazepam 20 mg, while zolpidem tartrate 10 mg effects were difficult to distinguish from placebo.

Because persons with a history of addiction to, or abuse of, drugs or alcohol are at increased risk for misuse, abuse and addiction of zolpidem, they should be monitored carefully when receiving zolpidem or any other hypnotic.

9.3 Dependence

Use of Zolpidem Tartrate may lead to development of physical and/or psychological dependence. This risk of dependence increases with dose and duration of treatment. The risk of abuse and dependence is also greater in patients with history of alcohol or drug abuse. Zolpidem Tartrate should be used with extreme caution in patients with current or past alcohol or drug abuse.

Physical dependence is a state of adaptation that is manifested by a specific withdrawal syndrome that can be produced by abrupt cessation, rapid dose reduction, decreasing blood level of the drug, and/or administration of an antagonist.

Sedative/hypnotics have produced withdrawal signs and symptoms following abrupt discontinuation. These reported symptoms range from mild dysphoria and insomnia to a withdrawal syndrome that may include abdominal and muscle cramps, vomiting, sweating, tremors, convulsions, and delirium.

The following adverse events, which are considered to meet the DSM-III-R criteria for uncomplicated sedative/hypnotic withdrawal, were reported during Zolpidem Tartrate clinical trials following placebo substitution occurring within 48 hours following last zolpidem treatment: fatigue, nausea, flushing, lightheadedness, uncontrolled crying, emesis, stomach cramps, panic attack, nervousness, and abdominal discomfort. These reported adverse events occurred at an incidence of 1% or less. However, available data cannot provide a reliable estimate of the incidence, if any, of dependence during treatment at recommended doses. There have been postmarketing reports of abuse, dependence and withdrawal with zolpidem.

10 OVERDOSAGE

10.1 Signs and Symptoms

In postmarketing experience of overdose with zolpidem tartrate alone, or in combination with CNS-depressant agents, impairment of consciousness ranging from somnolence to coma, cardiovascular and/or respiratory compromise, and fatal outcomes have been reported.

10.2 Recommended Treatment

General symptomatic and supportive measures should be used along with immediate gastric lavage where appropriate. Intravenous fluids should be administered as needed. Zolpidem's sedative hypnotic effect was shown to be reduced by flumazenil and therefore may be useful; however, flumazenil administration may contribute to the appearance of neurological symptoms (convulsions). As in all cases of drug overdose, respiration, pulse, blood pressure, and other appropriate signs should be monitored and general supportive measures employed. Hypotension and CNS depression should be monitored and treated by appropriate medical intervention. Sedating drugs should be withheld following zolpidem overdosage, even if excitation occurs. The value of dialysis in the treatment of overdosage has not been determined, although hemodialysis studies in patients with renal failure receiving therapeutic doses have demonstrated that zolpidem is not dialyzable.

As with the management of all overdosage, the possibility of multiple drug ingestion should be considered. The physician may wish to consider contacting a poison control center for up-to-date information on the management of hypnotic drug product overdosage.

11 DESCRIPTION

Zolpidem Tartrate contains zolpidem tartrate, a gamma-aminobutyric acid (GABA) A receptor positive modulator of the imidazopyridine class. Zolpidem Tartrate extended-release tablets is available in 6.25 mg and 12.5 mg strength tablets for oral administration.

Chemically, zolpidem is N,N,6-trimethyl-2-p-tolylimidazo[1,2-a] pyridine-3-acetamide L-(+)-tartrate (2:1). It has the following structure:

Zolpidem tartrate is a white to off-white crystalline powder that is sparingly soluble in water, alcohol, and propylene glycol. It has a molecular weight of 764.88.

Zolpidem Tartrate consists of a coated two-layer tablet: one layer that releases its drug content immediately and another layer that allows a slower release of additional drug content. The 6.25 mg Zolpidem Tartrate tablet contains the following inactive ingredients: colloidal silicon dioxide, hypromellose, lactose monohydrate, magnesium stearate, microcrystalline cellulose, polyethylene glycol, potassium bitartrate, red ferric oxide, sodium starch glycolate, and titanium dioxide. The 12.5 mg Zolpidem Tartrate tablet contains the following inactive ingredients: colloidal silicon dioxide, FD&C Blue #2, hypromellose, lactose monohydrate, magnesium stearate, microcrystalline cellulose, polyethylene glycol, potassium bitartrate, sodium starch glycolate, titanium dioxide, and yellow ferric oxide.

12 CLINICAL PHARMACOLOGY

12.1 Mechanism of Action

Zolpidem is a GABA A receptor positive modulator presumed to exert its therapeutic effects in the short-term treatment of insomnia through binding to the benzodiazepine site of α1 subunit containing GABA A receptors, increasing the frequency of chloride channel opening resulting in the inhibition of neuronal excitation.

12.2 Pharmacodynamics

Zolpidem binds to GABA A receptors with greater affinity for α1 subunit relative to α2 and α3 subunit containing receptors. Zolpidem has no appreciable binding affinity for α5 subunit containing GABA A receptors. This binding profile may explain the relative absence of myorelaxant effects in animal studies. Zolpidem has no appreciable binding affinity for dopaminergic D2, serotonergic 5HT2, adrenergic, histaminergic or muscarinic receptors.

12.3 Pharmacokinetics

Zolpidem Tartrate exhibits biphasic absorption characteristics, which results in rapid initial absorption from the gastrointestinal tract similar to zolpidem tartrate immediate-release, then provides extended plasma concentrations beyond three hours after administration. A study in 24 healthy male subjects was conducted to compare mean zolpidem plasma concentration-time profiles obtained after single oral administration of Zolpidem Tartrate 12.5 mg and of an immediate-release formulation of zolpidem tartrate (10 mg). The terminal elimination half-life observed with Zolpidem Tartrate (12.5 mg) was similar to that obtained with immediate-release zolpidem tartrate (10 mg). The mean plasma concentration-time profiles are shown in Figure 1.

Figure 1: Mean Plasma Concentration-Time Profiles for Zolpidem Tartrate (12.5 mg) and Immediate-Release Zolpidem Tartrate (10 mg)

In adult and elderly patients treated with Zolpidem Tartrate, there was no evidence of accumulation after repeated once-daily dosing for up to two weeks.

Absorption

Following administration of Zolpidem Tartrate, administered as a single 12.5 mg dose in healthy male adult subjects, the mean peak concentration (Cmax) of zolpidem was 134 ng/mL (range: 68.9 to 197 ng/ml) occurring at a median time (Tmax) of 1.5 hours. The mean AUC of zolpidem was 740 ng∙hr/mL (range: 295 to 1359 ng∙hr/mL).

A food-effect study in 45 healthy subjects compared the pharmacokinetics of Zolpidem Tartrate 12.5 mg when administered while fasting or within 30 minutes after a meal. Results demonstrated that with food, mean AUC and Cmaxwere decreased by 23% and 30%, respectively, while median Tmaxwas increased from 2 hours to 4 hours. The half-life was not changed. These results suggest that, for faster sleep onset, Zolpidem Tartrate should not be administered with or immediately after a meal.

Distribution

Total protein binding was found to be 92.5 ± 0.1% and remained constant, independent of concentration between 40 and 790 ng/mL.

Metabolism

Zolpidem is converted to inactive metabolites that are eliminated primarily by renal excretion.

Elderly

In 24 elderly (≥65 years) healthy subjects administered a single 6.25 mg dose of Zolpidem Tartrate, the mean peak concentration (Cmax) of zolpidem was 70.6 (range: 35.0 to 161) ng/mL occurring at a median time (Tmax) of 2.0 hours. The mean AUC of zolpidem was 413 ng∙hr/mL (range: 124 to 1190 ng∙hr/mL) and the mean elimination half-life was 2.9 hours (range: 1.59 to 5.50 hours).

Hepatic impairment

Zolpidem Tartrate was not studied in patients with hepatic impairment. The pharmacokinetics of an immediate-release formulation of zolpidem tartrate in eight patients with chronic hepatic insufficiency was compared to results in healthy subjects. Following a single 20 mg oral zolpidem tartrate dose, mean Cmaxand AUC were found to be two times (250 vs 499 ng/mL) and five times (788 vs 4,203 ng∙hr/mL) higher, respectively, in hepatically compromised patients. Tmaxdid not change. The mean half-life in cirrhotic patients of 9.9 hr (range: 4.1 to 25.8 hr) was greater than that observed in normal subjects of 2.2 hr (range: 1.6 to 2.4 hr) [see Dosage and Administration (2.2), Warnings and Precautions (5.8), Use in Specific Populations (8.7)] .

Renal impairment

Zolpidem Tartrate was not studied in patients with renal impairment. The pharmacokinetics of an immediate-release formulation of zolpidem tartrate were studied in 11 patients with end-stage renal failure (mean ClCr= 6.5 ± 1.5 mL/min) undergoing hemodialysis three times a week, who were dosed with zolpidem tartrate 10 mg orally each day for 14 or 21 days. No statistically significant differences were observed for Cmax, Tmax, half-life, and AUC between the first and last day of drug administration when baseline concentration adjustments were made. Zolpidem was not hemodialyzable. No accumulation of unchanged drug appeared after 14 or 21 days. Zolpidem pharmacokinetics was not significantly different in renally impaired patients. No dosage adjustment is necessary in patients with compromised renal function.

Elimination

When Zolpidem Tartrate was administered as a single 12.5 mg dose in healthy male adult subjects, the mean zolpidem elimination half-life was 2.8 hours (range: 1.62 to 4.05 hr).

CNS depressants

Coadministration of zolpidem with other CNS depressants increases the risk of CNS depression [see Warnings and Precautions (5.2)]. Zolpidem tartrate was evaluated in healthy volunteers in single-dose interaction studies for several CNS drugs. Imipramine in combination with zolpidem produced no pharmacokinetic interaction other than a 20% decrease in peak levels of imipramine, but there was an additive effect of decreased alertness. Similarly, chlorpromazine in combination with zolpidem produced no pharmacokinetic interaction, but there was an additive effect of decreased alertness and psychomotor performance.

A study involving haloperidol and zolpidem revealed no effect of haloperidol on the pharmacokinetics or pharmacodynamics of zolpidem. The lack of a drug interaction following single-dose administration does not predict the absence of an effect following chronic administration.

An additive adverse effect on psychomotor performance between alcohol and oral zolpidem was demonstrated [see Warnings and Precautions (5.2)].

Following five consecutive nightly doses at bedtime of oral zolpidem tartrate 10 mg in the presence of sertraline 50 mg (17 consecutive daily doses, at 7:00 am, in healthy female volunteers), zolpidem Cmaxwas significantly higher (43%) and Tmaxwas significantly decreased (-53%). Pharmacokinetics of sertraline and N-desmethylsertraline were unaffected by zolpidem.

A single-dose interaction study with zolpidem tartrate 10 mg and fluoxetine 20 mg at steady-state levels in male volunteers did not demonstrate any clinically significant pharmacokinetic or pharmacodynamic interactions. When multiple doses of zolpidem and fluoxetine were given at steady state and the concentrations evaluated in healthy females, an increase in the zolpidem half-life (17%) was observed. There was no evidence of an additive effect in psychomotor performance.

Drugs that affect drug metabolism via cytochrome P450

Some compounds known to inhibit CYP3A may increase exposure to zolpidem. The effect of inhibitors of other P450 enzymes on the pharmacokinetics of zolpidem is unknown.

A single-dose interaction study with zolpidem tartrate 10 mg and itraconazole 200 mg at steady-state levels in male volunteers resulted in a 34% increase in AUC0–∞of zolpidem tartrate. There were no pharmacodynamic effects of zolpidem detected on subjective drowsiness, postural sway, or psychomotor performance.

A single-dose interaction study with zolpidem tartrate 10 mg and rifampin 600 mg at steady-state levels in female subjects showed significant reductions of the AUC (-73%), Cmax(-58%), and T1/2(-36%) of zolpidem together with significant reductions in the pharmacodynamic effects of zolpidem tartrate. Rifampin, a CYP3A4 inducer, significantly reduced the exposure to and the pharmacodynamic effects of zolpidem [see Drug Interactions (7.2)] .

Similarly, St. John's wort, a CYP3A4 inducer, may also decrease the blood levels of zolpidem.

A single-dose interaction study with zolpidem tartrate 5 mg and ketoconazole, a potent CYP3A4 inhibitor, given as 200 mg twice daily for 2 days increased Cmaxof zolpidem (30%) and the total AUC of zolpidem (70%) compared to zolpidem alone and prolonged the elimination half-life (30%) along with an increase in the pharmacodynamic effects of zolpidem [see Drug Interactions (7.2)] .

Additionally, fluvoxamine (a strong inhibitor of CYP1A2 and a weak inhibitor of CYP3A4 and CYP2C9) and ciprofloxacin (a strong inhibitor of CYP1A2 and a moderate inhibitor of CYP3A4) are also likely to inhibit zolpidem's metabolic pathways, potentially leading to an increase in zolpidem exposure.

Other drugs with no interactions with zolpidem

A study involving cimetidine/zolpidem tartrate and ranitidine/zolpidem tartrate combinations revealed no effect of either drug on the pharmacokinetics or pharmacodynamics of zolpidem.

Zolpidem tartrate had no effect on digoxin pharmacokinetics and did not affect prothrombin time when given with warfarin in healthy subjects.

Special Populations

Drug Interactions

13 NONCLINICAL TOXICOLOGY

13.1 Carcinogenesis, Mutagenesis, Impairment of Fertility

Carcinogenesis

Zolpidem was administered to mice and rats for 2 years at oral doses of 4, 18, and 80 mg base/kg/day. In mice, these doses are approximately 2, 9, and 40 times the MRHD of 12.5 mg/day (10 mg zolpidem base) based on mg/m^2body surface area and in rats, these doses are approximately 4, 18, and 80 times the MRHD based on mg/m^2body surface area. No evidence of carcinogenic potential was observed in mice. In rats, renal tumors (lipoma, liposarcoma) were seen at the mid and high doses.

Mutagenesis

Zolpidem was negative in in vitro(bacterial reverse mutation, mouse lymphoma, and chromosomal aberration) and in vivo(mouse micronucleus) genetic toxicology assays.

Impairment of Fertility

Zolpidem was administered to rats at 4, 20, and 100 mg base/kg/day, which are approximately 4, 20, and 100 times the MRHD of 12.5 mg/day (10 mg zolpidem base) based on mg/m^2body surface area, prior to and during mating, and continuing in females through postpartum day 25. Zolpidem caused irregular estrus cycles and prolonged precoital intervals at the highest dose tested, which is approximately 100 times the MRHD based on mg/m^2body surface area. The NOAEL for these effects is 20 times the MRHD based on mg/m^2body surface area. There was no impairment of fertility at any dose tested.

14 CLINICAL STUDIES

14.1 Controlled Clinical Trials

Zolpidem Tartrate was evaluated in three placebo-controlled studies for the treatment of patients with chronic primary insomnia (as defined in the APA Diagnostic and Statistical Manual of Mental Disorders, DSM IV™).

Adult outpatients (18–64 years) with primary insomnia (N=212) were evaluated in a double-blind, randomized, parallel-group, 3-week trial comparing Zolpidem Tartrate 12.5 mg and placebo. Zolpidem Tartrate 12.5 mg decreased wake time after sleep onset (WASO) for the first 7 hours during the first 2 nights and for the first 5 hours after 2 weeks of treatment. Zolpidem Tartrate 12.5 mg was superior to placebo on objective measures (polysomnography recordings) of sleep induction (by decreasing latency to persistent sleep [LPS]) during the first 2 nights of treatment and after 2 weeks of treatment. Zolpidem Tartrate 12.5 mg was also superior to placebo on the patient reported global impression regarding the aid to sleep after the first 2 nights and after 3 weeks of treatment.

Elderly outpatients (≥65 years) with primary insomnia (N=205) were evaluated in a double-blind, randomized, parallel-group, 3-week trial comparing Zolpidem Tartrate 6.25 mg and placebo. Zolpidem Tartrate 6.25 mg decreased wake time after sleep onset (WASO) for the first 6 hours during the first 2 nights and the first 4 hours after 2 weeks of treatment. Zolpidem Tartrate 6.25 mg was superior to placebo on objective measures (polysomnography recordings) of sleep induction (by decreasing LPS) during the first 2 nights of treatment and after 2 weeks on treatment. Zolpidem Tartrate 6.25 mg was superior to placebo on the patient reported global impression regarding the aid to sleep after the first 2 nights and after 3 weeks of treatment.

In both studies, in patients treated with Zolpidem Tartrate, polysomnography showed increased wakefulness at the end of the night compared to placebo-treated patients.

In a 24-week double-blind, placebo controlled, randomized study in adult outpatients (18–64 years) with primary insomnia (N=1025), Zolpidem Tartrate 12.5 mg administered as needed (3 to 7 nights per week) was superior to placebo over 24 weeks, on patient global impression regarding aid to sleep, and on patient-reported specific sleep parameters for sleep induction and sleep maintenance with no significant increased frequency of drug intake observed over time.

14.2 Studies Pertinent to Safety Concerns for Sedative/Hypnotic Drugs

Next-Day Residual Effects

In five clinical studies (three controlled studies in adults [18–64 years of age] administered Zolpidem Tartrate 12.5 mg and two controlled studies in the elderly [≥65 years of age] administered Zolpidem Tartrate 6.25 mg or 12.5 mg), the effect of Zolpidem Tartrate on vigilance, memory, or motor function were assessed using neurocognitive tests. In these studies, no significant decrease in performance was observed eight hours after a nighttime dose. In addition, no evidence of next-day residual effects was detected with Zolpidem Tartrate 12.5 mg and 6.25 mg using self-ratings of sedation.

During the 3-week studies, next-day somnolence was reported by 15% of the adult patients who received 12.5 mg Zolpidem Tartrate versus 2% of the placebo group; next-day somnolence was reported by 6% of the elderly patients who received 6.25 mg Zolpidem Tartrate versus 5% of the placebo group [see Adverse Reactions (6)] . In a 6-month study, the overall incidence of next-day somnolence was 5.7% in the Zolpidem Tartrate group as compared to 2% in the placebo group.

Rebound Effects

Rebound insomnia, defined as a dose-dependent worsening in sleep parameters (latency, sleep efficiency, and number of awakenings) compared with baseline following discontinuation of treatment, is observed with short- and intermediate-acting hypnotics. In the two 3-week placebo-controlled studies in patients with primary insomnia, a rebound effect was only observed on the first night after abrupt discontinuation of Zolpidem Tartrate. On the second night, there was no worsening compared to baseline in the Zolpidem Tartrate group.

In a 6-month placebo-controlled study in which Zolpidem Tartrate was taken as needed (3 to 7 nights per week), within the first month a rebound effect was observed for Total Sleep Time (not for WASO) during the first night off medication. After this first month period, no further rebound insomnia was observed. After final treatment discontinuation no rebound was observed.

16 HOW SUPPLIED/STORAGE AND HANDLING

Zolpidem Tartrate 6.25 mg extended-release tablets are composed of two layers* and are coated, pink, round, biconvex, debossed with A~ on one side and supplied as:

NDC Number | Size
51407-761-01 | bottle of 100

Zolpidem Tartrate 12.5 mg extended-release tablets are composed of two layers* and are coated, blue, round, biconvex, debossed with A~ on one side and supplied as:

NDC Number | Size
51407-762-01 | bottle of 100

*Layers are covered by the coating and are indistinguishable.

STORAGE AND HANDLING

Store between 15°C–25°C (59°F–77°F). Limited excursions permissible up to 30°C (86°F).

17 PATIENT COUNSELING INFORMATION

Advise the patient to read the FDA-approved patient labeling (Medication Guide).

Inform patients and their families about the benefits and risks of treatment with Zolpidem Tartrate. Inform patients of the availability of a Medication Guide and instruct them to read the Medication Guide prior to initiating treatment with Zolpidem Tartrate and with each prescription refill. Review the Zolpidem Tartrate Medication Guide with every patient prior to initiation of treatment. Instruct patients or caregivers that Zolpidem Tartrate should be taken only as prescribed.

Complex Sleep Behaviors

Instruct patients and their families that Zolpidem Tartrate may cause complex sleep behaviors, including sleep-walking, sleep-driving, preparing and eating food, making phone calls, or having sex while not being fully awake. Serious injuries and death have occurred during complex sleep behavior episodes. Tell patients to discontinue Zolpidem Tartrate and notify their healthcare provider immediately if they develop any of these symptoms [see Boxed Warning, Warnings and Precautions (5.1)] .

CNS-Depressant Effects and Next-Day Impairment

Tell patients that Zolpidem Tartrate can cause next-day impairment even when used as prescribed, and that this risk is increased if dosing instructions are not carefully followed. Caution patients against driving and other activities requiring complete mental alertness the day after use. Inform patients that impairment can be present despite feeling fully awake. Advise patients that increased drowsiness and decreased consciousness may increase the risk of falls in some patients [see Warnings and Precautions (5.2)] .

Severe Anaphylactic and Anaphylactoid Reactions

Inform patients that severe anaphylactic and anaphylactoid reactions have occurred with zolpidem. Describe the signs/symptoms of these reactions and advise patients to seek medical attention immediately if any of them occur [see Warnings and Precautions (5.4)] .

Suicide

Tell patients to immediately report any suicidal thoughts.

Alcohol and other Drugs

Ask patients about alcohol consumption, medicines they are taking, and drugs they may be taking without a prescription. Advise patients not to use Zolpidem Tartrate if they drank alcohol that evening or before bed.

Concomitant Use with Opioids

Inform patients and caregivers that potentially serious additive effects may occur if Zolpidem Tartrate is used with opioids and not to use such drugs concomitantly unless supervised by a healthcare provider [Warnings and Precautions (5.2, 5.7), Drug Interactions (7.1)].

Tolerance, Abuse, and Dependence

Tell patients not to increase the dose of Zolpidem Tartrate on their own, and to inform you if they believe the drug "does not work."

Administration Instructions

Patients should be counseled to take Zolpidem Tartrate right before they get into bed and only when they are able to stay in bed a full night (7–8 hours) before being active again. Zolpidem Tartrate tablets should not be taken with or immediately after a meal. Advise patients NOT to take Zolpidem Tartrate if they drank alcohol that evening.

Pregnancy

Advise patients to notify their healthcare provider if they become pregnant or intend to become pregnant during treatment with Zolpidem Tartrate. Advise patients that use of Zolpidem Tartrate late in the third trimester may cause respiratory depression and sedation in neonates. Advise mothers who used Zolpidem Tartrate during the late third trimester of pregnancy to monitor neonates for signs of sleepiness (more than usual), breathing difficulties, or limpness [see Use in Specific Populations (8.1)].

Lactation

Advise breastfeeding mothers using Zolpidem Tartrate to monitor infants for increased sleepiness (more than usual), breathing difficulties, or limpness. Instruct breastfeeding mothers to seek immediate medical care if they notice these signs. A lactating woman may consider pumping and discarding breastmilk during treatment and for 23 hours after Zolpidem Tartrate administration to minimize drug exposure to a breastfed infant [see Use in Specific Populations (8.2)] .

Marketed by:
GSMS, Inc.
Camarillo, CA 93012 USA

MEDICATION GUIDE
Zolpidem Tartrate
extended-release tablets, for oral use, C-IV

What is the most important information I should know about Zolpidem Tartrate?
Zolpidem Tartrate may cause serious side effects, including:

- Complex sleep behaviors.After taking Zolpidem Tartrate, you may get up out of bed while not being fully awake and do an activity that you do not know you are doing. The next morning, you may not remember that you did anything during the night. These activities may happen with Zolpidem Tartrate whether or not you drink alcohol or take other medicines that make you sleepy. Some of these complex sleep behaviors have caused serious injury and death. People taking Zolpidem Tartrate have reported:
  - sleep-walking
  - sleep-driving
  - making and eating food
  - talking on the phone
  - having sex
  Stop taking Zolpidem Tartrate and tell your healthcare provider right away if you find out that you have done any of the above activities after taking Zolpidem Tartrate.

What is Zolpidem Tartrate?
Zolpidem Tartrate is a prescription sleep medicine used for the treatment of adults who have trouble falling asleep or staying asleep (insomnia).

- It is not known if Zolpidem Tartrate is safe and effective in children under the age of 18 years. Zolpidem Tartrate is not recommended for use in children under the age of 18 years.
- Zolpidem Tartrate is a federally controlled substance (C-IV) because it can be abused or lead to dependence.Keep Zolpidem Tartrate in a safe place to protect it from theft. Never give your Zolpidem Tartrate to anyone else because it can cause death or harm them. Selling or giving away this medicine is against the law.

Do not take Zolpidem Tartrate if you:

- have had complex sleep behaviors that happened after taking Zolpidem Tartrate in the past. See " What is the most important information I should know about Zolpidem Tartrate?
- are allergic to zolpidem or any of the ingredients in Zolpidem Tartrate. See the end of this Medication Guide for a complete list of ingredients in Zolpidem Tartrate.

Before taking Zolpidem Tartrate, tell your healthcare provider about all of your medical conditions, including if you:

- have a history of depression, mental illness, or suicidal thoughts or actions
- have a history of drug or alcohol abuse or addiction
- have kidney or liver disease
- have a lung disease or breathing problems
- have sleep apnea
- have myasthenia gravis
- are pregnant or plan to become pregnant. Taking Zolpidem Tartrate in the third trimester of pregnancy may harm your unborn baby.
  - Tell your healthcare provider if you become pregnant or plan to become pregnant during treatment with Zolpidem Tartrate.
  - Babies born to mothers who take Zolpidem Tartrate during the third trimester of pregnancy may have symptoms of breathing problems and sedation (such as sleepiness or low muscle tone).
- are breastfeeding or plan to breastfeed. Zolpidem Tartrate passes into your breast milk. Talk to your healthcare provider about the best way to feed your baby while you take Zolpidem Tartrate.

Tell your healthcare provider about all of the medicines you take, including prescription and over-the-counter medicines, vitamins, and herbal supplements.
Zolpidem Tartrate and other medicines can interact with each other causing serious side effects. Zolpidem Tartrate may affect the way other medicines work, and other medicines may affect how Zolpidem Tartrate works.
Especially tell your healthcare provider if you:

- take benzodiazepines
- take opioids as it may increase the risk of breathing problems (respiratory depression).
- take tricyclic antidepressants
- take other medicines that can make you sleepy or affect your breathing (including other zolpidem medicines)
- drink alcohol

You can ask your pharmacist for a list of medicines that interact with Zolpidem Tartrate.
Know the medicines you take. Keep a list of them to show your healthcare provider and pharmacist when you get a new medicine.

How should I take Zolpidem Tartrate?

- Take Zolpidem Tartrate exactly as prescribed.Do not change your dose on your own. Tell your healthcare provider if you think Zolpidem Tartrate is not working for you.
- Zolpidem Tartrate is for short-term use only.Treatment with Zolpidem Tartrate should be as short as possible because the risk of dependence increases the longer you are being treated.
- Take 1 Zolpidem Tartrate tablet a night right before bedtime.
- Do not take Zolpidem Tartrate if you are not able to stay in bed a full night (7 to 8 hours) before you must be active again.
- You should not take Zolpidem Tartrate with or right after a meal. Zolpidem Tartrate may help you fall asleep faster if you take it on an empty stomach.
- Do not take Zolpidem Tartrate if you drank alcohol that evening or before bed.
- Swallow Zolpidem Tartrate tablets whole. Do not divide, crush, or chew Zolpidem Tartrate tablets. If you cannot swallow Zolpidem Tartrate tablets whole, tell your healthcare provider. You may need a different medicine.
- Call your healthcare provider if your sleep problems get worse or do not get better within 7 to 10 days. This may mean that there is another condition causing your sleep problems.
- If you take too much Zolpidem Tartrate, call your healthcare provider or go to the nearest hospital emergency room right away.

What are the possible side effects of Zolpidem Tartrate?
Zolpidem Tartrate may cause serious side effects including:

- See " What is the most important information I should know about Zolpidem Tartrate?"
- Zolpidem Tartrate can make you sleepy or dizzy and can slow your thinking and motor skills. Next-day sleepiness is common, but can be serious. Because Zolpidem Tartrate can make you sleepy or dizzy you are at a higher risk for falls.
  - Do not drive, operate heavy machinery, or do other dangerous activities until you know how Zolpidem Tartrate affects you.
  - Do not drink alcohol or take opioids or other medicines that may make you sleepy or dizzy while taking Zolpidem Tartrate without first talking to your healthcare provider. When taken with alcohol or other medicines that cause sleepiness or dizziness, Zolpidem Tartrate may make your sleepiness or dizziness much worse.
- Severe allergic reactions.Symptoms include swelling of the tongue or throat, trouble breathing, and nausea and vomiting. Get emergency medical help if you get these symptoms after taking Zolpidem Tartrate.
- Abnormal thoughts and behavior.Symptoms include more outgoing or aggressive behavior than normal, confusion (delirium), acting strangely, agitation, hallucinations, worsening of depression, and suicidal thoughts or actions.
- Risk of suicide and worsening of depression.Worsening of depression, including suicidal thoughts and actions can happen during treatment with medicines like Zolpidem Tartrate. Call your healthcare provider right away if you develop any thoughts of suicide, dying, or worsening depression during treatment with Zolpidem Tartrate.
- Breathing problems.See " Before taking Zolpidem Tartrate, tell your healthcare provider about all of your medical conditions, including if you:" Call your healthcare provider or get emergency medical help right away if you develop breathing problems during treatment with Zolpidem Tartrate.
- Problems with your nervous system caused by severe liver disease (hepatic encephalopathy).
- Withdrawal symptoms.You may have withdrawal symptoms if you stop taking Zolpidem Tartrate suddenly. Withdrawal symptoms can be serious and include stomach and muscle cramps, vomiting, sweating, shakiness, seizures, and confusion (delirium). Talk to your healthcare provider about slowly stopping Zolpidem Tartrate to avoid withdrawal symptoms.

The most common side effects of Zolpidem Tartrate includeheadache and dizziness.
These are not all the side effects of Zolpidem Tartrate.
Call your doctor for medical advice about side effects. You may report side effects to FDA at 1–800–FDA–1088.

How should I store Zolpidem Tartrate?

- Store Zolpidem Tartrate between at room temperature between 68°F to 77°F (20°C to 25°C).

Keep Zolpidem Tartrate and all medicines out of reach of children.

General Information about the safe and effective use of Zolpidem Tartrate.
Medicines are sometimes prescribed for purposes other than those listed in a Medication Guide. Do not use Zolpidem Tartrate for a condition for which it was not prescribed. Do not give Zolpidem Tartrate to other people, even if they have the same symptoms that you have. It may harm them. You can ask your healthcare provider or pharmacist for information about Zolpidem Tartrate that is written for healthcare professionals.

What are the ingredients in Zolpidem Tartrate?
Active Ingredient:zolpidem tartrate
Inactive Ingredients:
The 6.25 mg tablets contain: colloidal silicon dioxide, hypromellose, lactose monohydrate, magnesium stearate, microcrystalline cellulose, polyethylene glycol, potassium bitartrate, red ferric oxide, sodium starch glycolate, and titanium dioxide.
The 12.5 mg tablets contain: colloidal silicon dioxide, FD&C Blue #2, hypromellose, lactose monohydrate, magnesium stearate, microcrystalline cellulose, polyethylene glycol, potassium bitartrate, sodium starch glycolate, titanium dioxide, and yellow ferric oxide.

Marketed by:
GSMS, Inc.
Camarillo, CA 93012 USA

This Medication Guide has been approved by the U.S. Food and Drug Administration.

Revised: 9/2025

PRINCIPAL DISPLAY PANEL - 6.25 mg Tablet Bottle Label

NDC 51407-761-01

(ZOLPIDEM TARTRATE EXTENDED-RELEASE) CIV

6.25 mg Tablets

Dispense with Medication Guide

Rx only
100 Tablets

PRINCIPAL DISPLAY PANEL - 12.5 mg Tablet Bottle Label

NDC 51407-762-01

(ZOLPIDEM TARTRATE EXTENDED-RELEASE) CIV

12.5 mg Tablets

Dispense with Medication Guide

Rx only 100 Tablets